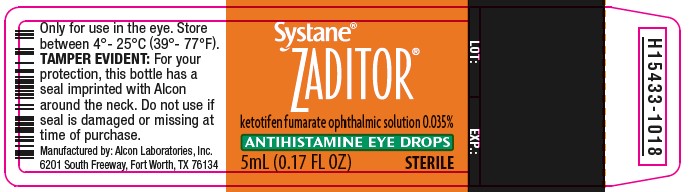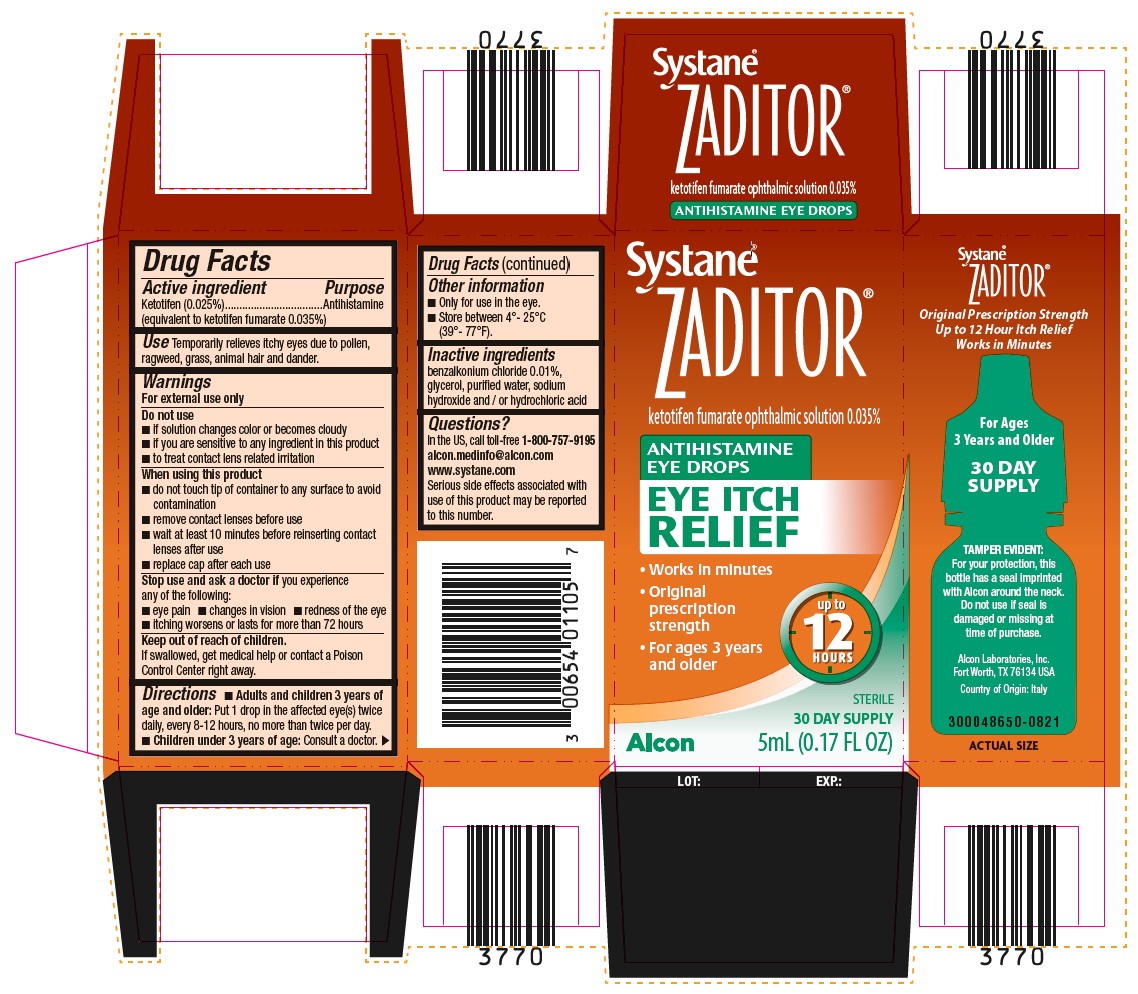 DRUG LABEL: Zaditor
NDC: 0065-4011 | Form: SOLUTION
Manufacturer: Alcon Laboratories, Inc.
Category: otc | Type: HUMAN OTC DRUG LABEL
Date: 20231215

ACTIVE INGREDIENTS: Ketotifen Fumarate .25 mg/1 mL
INACTIVE INGREDIENTS: Benzalkonium Chloride; Glycerin; Sodium Hydroxide; Hydrochloric Acid; Water

Drug Facts

ACTIVE INGREDIENT

Active ingredient | Purpose
Ketotifen (0.025%) (equivalent to ketotifen fumarate 0.035%) | Antihistamine

INDICATIONS AND USAGE

Use Temporarily relieves itchy eyes due to pollen, ragweed, grass, animal hair and dander.

Warnings

For external use only

Do Not Use

- if solution changes color or becomes cloudy
- if you are sensitive to any ingredient in this product
- to treat contact lens related irritation

When using this product

- do not touch tip of container to any surface to avoid contamination
- remove contact lenses before use
- wait at least 10 minutes before reinserting contact lenses after use
- replace cap after each use

Stop use and ask a doctor if you experience any of the following:

- eye pain
- changes in vision
- redness of the eye
- itching worsens or lasts for more than 72 hours

Keep out of reach of children.
If swallowed, get medical help or contact a Poison Control Center right away.

Directions

- Adults and children 3 years of age and older: Put 1 drop in the affected eye(s) twice daily, every 8-12 hours, no more than twice per day.
- Children under 3 years of age: Consult a doctor

Other information

- Only for use in the eye.
- Store between 4°-25°C (39°-77°F).

Inactive ingredients

benzalkonium chloride 0.01%, glycerol, purified water, sodium hydroxide and/or hydrochloric acid

Questions?

In the US, call toll-free 1-800-757-9195
alcon.medinfo@alcon.com
www.systane.com
Serious side effects associated with use of this product may be reported to this number.

PACKAGE LABEL.PRINCIPAL DISPLAY PANEL

Systane®
ZADITOR®
ketotifen fumarate ophthalmic solution 0.035%
ANTIHISTAMINE EYE DROPS
EYE ITCH RELIEF

- Works in minutes
- Original prescription strength
- For ages 3 years and older

up to 12 HOURS
Alcon
STERILE
30 DAY SUPPLY
5mL (0.17 FL OZ)
Systane®
ZADITOR®
Original Prescription Strength
Up to 12 Hour Itch Relief
Works in Minutes
For Ages 3 Years and Older
30 DAY SUPPLY
TAMPER EVIDENT: For your protection, this bottle has a seal imprinted with Alcon around the neck. Do not use if seal is damaged or missing at time of purchase.
Alcon Laboratories, Inc.
Fort Worth, TX 76134 USA
Country of Origin: Italy
300048650-0821
ACTUAL SIZE
LOT: EXP.:

Systane®
ZADITOR®
ketotifen fumarate ophthalmic solution 0.035%
ANTIHISTAMINE EYE DROPS
EYE ITCH RELIEF
5mL (0.17 FL OZ) STERILE
Only for use in the eye. Store between 4° - 25°C (39° - 77°F).
TAMPER EVIDENT: For your protection, this bottle has a seal imprinted with Alcon around the neck. Do not use if seal is damaged or missing at time of purchase.
Manufactured by:
Alcon Laboratories, Inc.
6201 South Freeway,
Fort Worth, TX 76134
H15433-1018